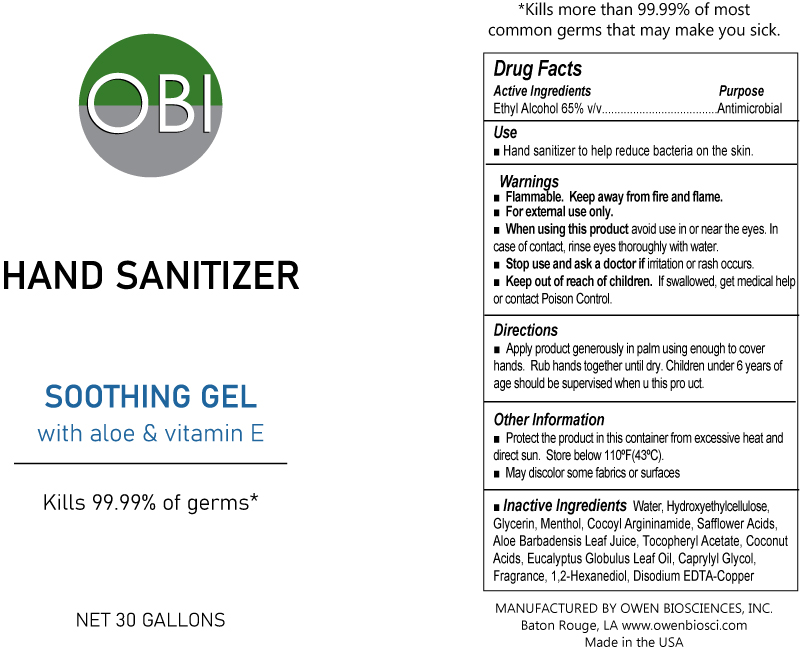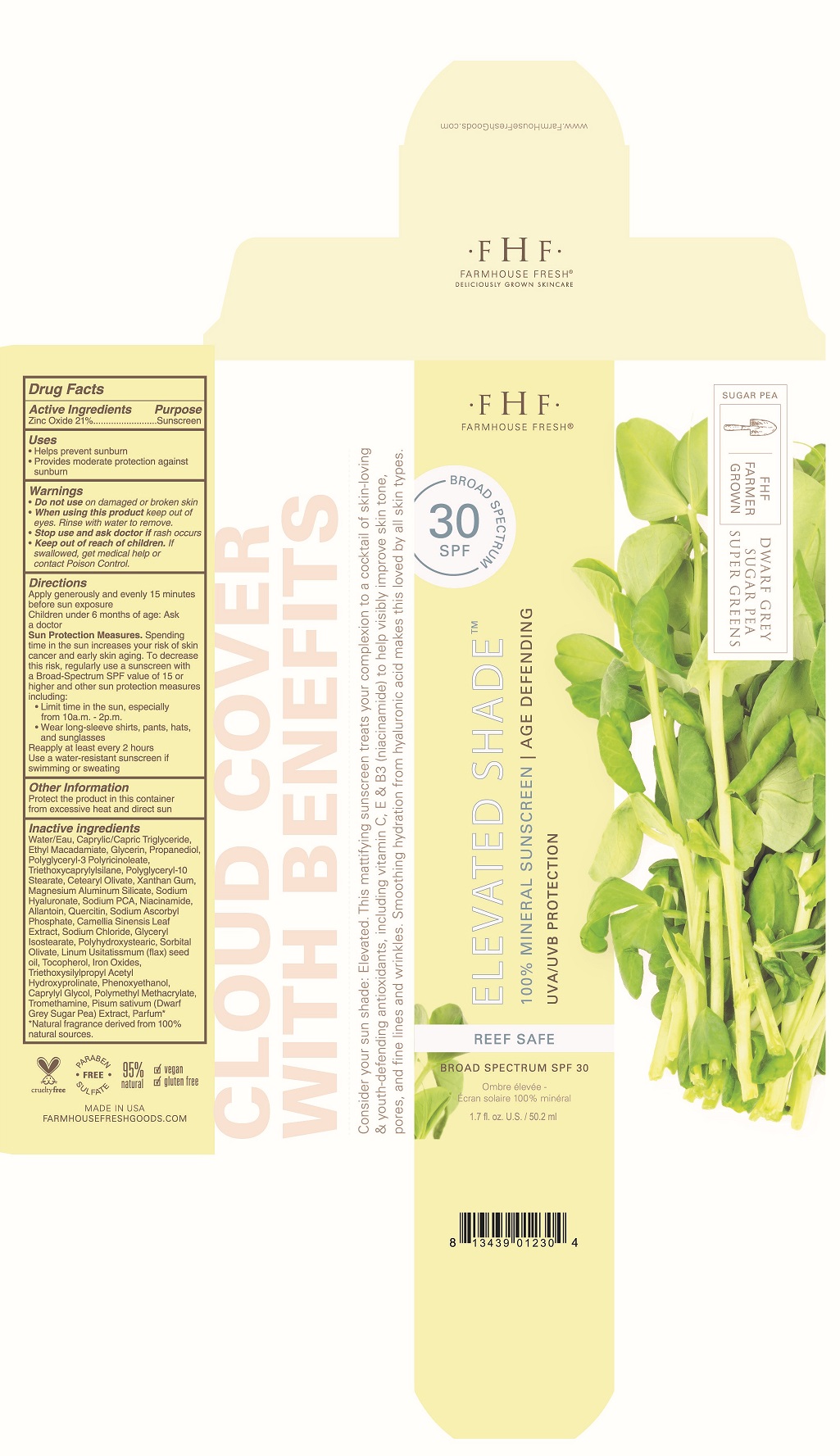 DRUG LABEL: Cream Oil Sunscreen
NDC: 59958-408 | Form: CREAM
Manufacturer: Owen Biosciences, Inc.
Category: otc | Type: HUMAN OTC DRUG LABEL
Date: 20241105

ACTIVE INGREDIENTS: ZINC OXIDE 21 g/100 g; TITANIUM DIOXIDE 1.25 g/100 g
INACTIVE INGREDIENTS: WATER 32.6 g/100 g

Cream Oil Sunscreen

Active Ingredients Purpose

Zinc Oxide 21.50%...... Sunscreen

Titanium Dioxide 1.25%...... Sunscreen

Uses

Helps protect against sunburn
provides moderate protection against sunburn

Warnings

Do not use on damaged or broken skin

When using this product keep out of eyes. Rinse with water to remove

Stop use and ask doctor if rash occurs

Keep out of reach of children If swallowed, get medicl help or contact poison control center.

Directions

Apply generously and evenly 15 minutes before sun exposure.
Children under 6 months of age: ask doctor.
Sun protection measures. Spending time in the sun increases your risk of skin cancer and early skin aging. To decrease the risk, regularly use a sunscreen with a Broad-Spectrum SPF value of 15 or higher and other sun protection measures including:
Limit time in the sun, especially from 10a.m. - 2p.m.
wear long sleeve shirts, pants, hats and sunglasses.
Reapply at least every 2 hours
Use a water-resistant sunscreen if swimming or sweating

Other Information

Protect the product in this contianer from heat and direct sun.

DOSAGE AND ADMINISTRATION

Apply generously and evenly 15 minutes before sun exposure.

Children under 6 months of age: ask doctor.

Sun protection measures. Spending time in the sun increases your risk of skin cancer and early skin aging. To decrease the risk, regularly use a sunscreen with a Broad-Spectrum SPF value of 15 or higher and other sun protection measures including:

Limit time in the sun, especially from 10a.m. - 2p.m.

wear long sleeve shirts, pants, hats and sunglasses.

Reapply at least every 2 hours

Use a water-resistant sunscreen if swimming or sweating

RECENT MAJOR CHANGES

Apply generously and evenly 15 minutes before sun exposure.

Children under 6 months of age: ask doctor.

Sun protection measures. Spending time in the sun increases your risk of skin cancer and early skin aging. To decrease the risk, regularly use a sunscreen with a Broad-Spectrum SPF value of 15 or higher and other sun protection measures including:

Limit time in the sun, especially from 10a.m. - 2p.m.

wear long sleeve shirts, pants, hats and sunglasses.

Reapply at least every 2 hours

Use a water-resistant sunscreen if swimming or sweating

Keep out of reach of children If swallowed, get medicl help or contact poison control center.

PURPOSE

Sunscreen